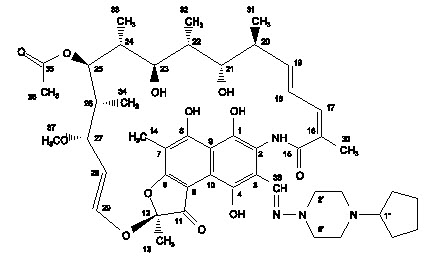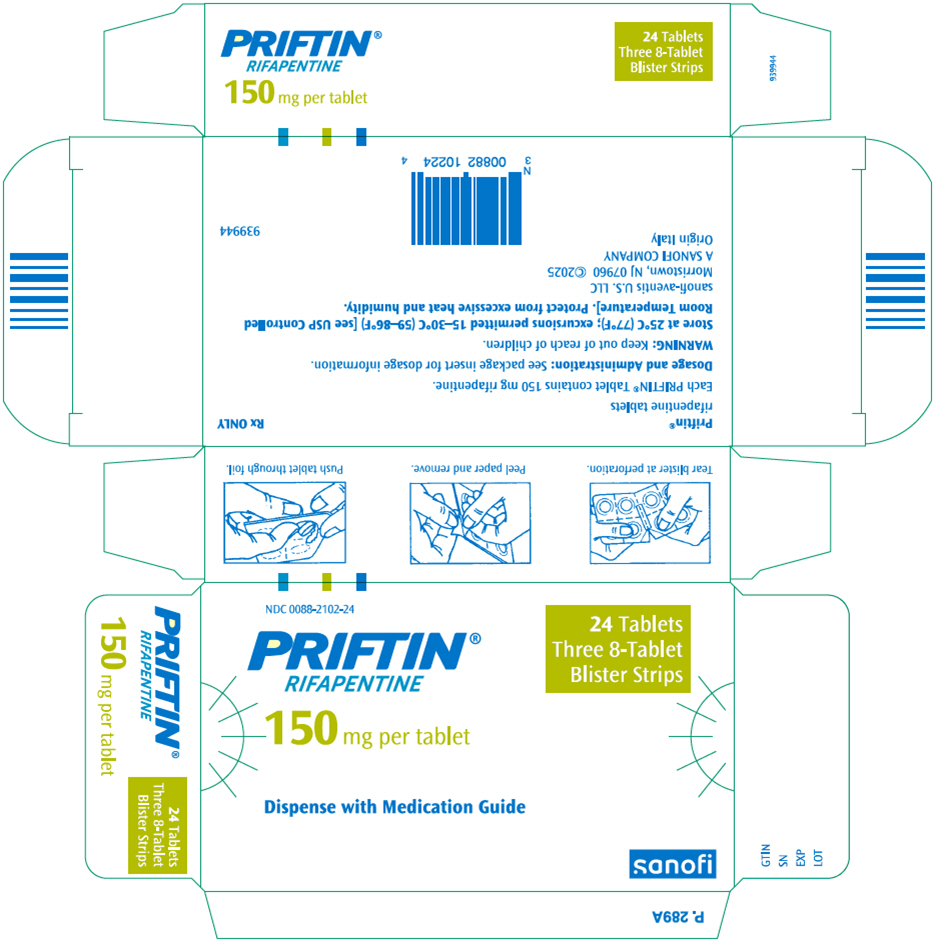 DRUG LABEL: Priftin
NDC: 0088-2102 | Form: TABLET, FILM COATED
Manufacturer: sanofi-aventis U.S. LLC
Category: prescription | Type: HUMAN PRESCRIPTION DRUG LABEL
Date: 20260206

ACTIVE INGREDIENTS: RIFAPENTINE 150 mg/1 1
INACTIVE INGREDIENTS: CALCIUM STEARATE; EDETATE DISODIUM; FD&C BLUE NO. 2; ALUMINUM OXIDE; HYDROXYPROPYL CELLULOSE (1600000 WAMW); HYPROMELLOSE, UNSPECIFIED; MICROCRYSTALLINE CELLULOSE; POLYETHYLENE GLYCOL, UNSPECIFIED; STARCH, CORN; PROPYLENE GLYCOL; SODIUM ASCORBATE; SODIUM LAURYL SULFATE; SODIUM STARCH GLYCOLATE TYPE A CORN; FERRIC OXIDE RED; TITANIUM DIOXIDE

HIGHLIGHTS OF PRESCRIBING INFORMATION

These highlights do not include all the information needed to use PRIFTIN® safely and effectively. See full prescribing information for PRIFTIN.
PRIFTIN (rifapentine) tablets, for oral use
Initial U.S. Approval: 1998

RECENT MAJOR CHANGES

Warnings and Precautions, Paradoxical Drug Reactions (5.5) | 01/2026

1 INDICATIONS AND USAGE

- PRIFTIN is a rifamycin antimycobacterial drug indicated in patients 12 years of age and older for the treatment of active pulmonary tuberculosis (TB) caused by Mycobacterium tuberculosis in combination with one or more antituberculosis (anti-TB) drugs to which the isolate is susceptible. (1.1)
- PRIFTIN is indicated for the treatment of latent tuberculosis infection (LTBI) caused by M. tuberculosis in combination with isoniazid in patients 2 years of age and older at high risk of progression to TB disease. (1.2)
- See Full Prescribing Information for Limitations of Use. (1.1, 1.2)

2 DOSAGE AND ADMINISTRATION

- Active pulmonary tuberculosis: PRIFTIN should be used in regimens consisting of an initial 2 month phase followed by a 4 month continuation phase. (2.1)
  Initial phase (2 Months): 600 mg twice weekly for two months as directly observed therapy (DOT), with no less than 72 hours between doses, in combination with other antituberculosis drugs. (2.1)
  Continuation phase (4 Months): 600 mg once weekly for 4 months as directly observed therapy with isoniazid or another appropriate antituberculosis agent. (2.1)
- Latent tuberculosis infection: PRIFTIN should be administered in combination with isoniazid once weekly for 12 weeks as directly observed therapy. (2.2)
  Adults and pediatric patients ≥12 years: PRIFTIN (based on weight, see table below) and isoniazid 15 mg/kg (900 mg maximum). (2.2)
  Pediatric patients 2 to 11 years: PRIFTIN (based on weight, see table below) and isoniazid 25 mg/kg (900 mg maximum). (2.2)
  Weight range | PRIFTIN dose | Number of PRIFTIN tablets
  10–14 kg | 300 mg | 2
  14.1–25 kg | 450 mg | 3
  25.1–32 kg | 600 mg | 4
  32.1–50 kg | 750 mg | 5
  >50 kg | 900 mg | 6
  For Latent Tuberculosis Infection, the maximum recommended dose of PRIFTIN is 900 mg once weekly for 12 weeks. (2.2)
- Take with food. Tablets may be crushed and added to semi-solid food. (2.3)

3 DOSAGE FORMS AND STRENGTHS

Tablets: 150 mg (3)

4 CONTRAINDICATIONS

Known hypersensitivity to any rifamycin. (4.1)

5 WARNINGS AND PRECAUTIONS

- Hepatotoxicity: Monitor for symptoms of liver injury and discontinue PRIFTIN if signs or symptoms or liver injury occur. (5.1)
- Hypersensitivity: Discontinue PRIFTIN if signs or symptoms of hypersensitivity reaction occur. (5.2)
- Severe cutaneous adverse reactions: Discontinue PRIFTIN at the first appearance of skin rash, mucosal lesions, or any other sign of hypersensitivity. (5.3)
- Relapse in the treatment of active pulmonary tuberculosis: Do not use as a once-weekly continuation phase regimen with isoniazid in HIV-infected patients. Monitor for signs or symptoms of relapse in patients with cavitary lesions or bilateral disease. (5.4, 14.1)
- Paradoxical Drug Reactions: If worsening of symptoms or signs occur during antimycobacterial treatment, consider paradoxical drug reaction in the differential diagnosis, and monitor or treat accordingly. (5.5)
- Drug Interactions: May interact with drugs metabolized by CYP450. (5.6, 7.1, 7.4)
- Discoloration of body fluids: May permanently stain contact lenses or dentures red-orange. (5.7)
- Clostridioides difficile–associated diarrhea: Evaluate if diarrhea occurs. (5.8)
- Porphyria: Avoid use in patients with porphyria. (5.9)

6 ADVERSE REACTIONS

The most common adverse reactions with regimen for active pulmonary tuberculosis (3% and greater) are anemia, lymphopenia, hemoptysis, neutropenia, cough, thrombocytosis, increased sweating, increased ALT, increased AST, back pain, rash, anorexia, arthralgia, increased blood urea, and headache. The most common adverse reaction (3% and greater) with the regimen for latent tuberculosis infection is hypersensitivity reaction. (6.1)
To report SUSPECTED ADVERSE REACTIONS, contact sanofi-aventis U.S. LLC at 1-800-633-1610 or FDA at 1-800-FDA-1088 or www.fda.gov/medwatch.

7 DRUG INTERACTIONS

- Protease Inhibitors and Reverse Transcriptase Inhibitors. (5.2, 7.1)
- Hormonal Contraceptives: Use an effective non-hormonal method of contraception or add a barrier method of contraception during treatment with PRIFTIN. (7.3)
- May increase metabolism and decrease the activity of drugs metabolized by cytochrome P450 3A4 and 2C8/9. Dosage adjustments may be necessary if given concomitantly. (7.4)

8 USE IN SPECIFIC POPULATIONS

- Pregnancy: Based on animal data, may cause fetal harm. (8.1)
- Lactation: Monitor infants exposed to PRIFTIN through breast milk for irritability, prolonged unexplained crying, yellowing of the eyes, changes in color of the urine or stool. (8.2)
- Pediatrics: Safety and effectiveness in treating active pulmonary tuberculosis in pediatric patients under the age of 12 years have not been established. (8.4)

FULL PRESCRIBING INFORMATION

1 INDICATIONS AND USAGE

1.1 Active Pulmonary Tuberculosis

PRIFTIN® (rifapentine) is indicated in adults and pediatric patients 12 years and older for the treatment of active pulmonary tuberculosis (TB) caused by Mycobacterium tuberculosis. PRIFTIN must always be used in combination with one or more antituberculosis (anti-TB) drugs to which the isolate is susceptible [see Dosage and Administration (2.1) and Clinical Studies (14.1)].

Limitations of Use

Do not use PRIFTIN monotherapy in either the initial or the continuation phases of active antituberculous treatment.

PRIFTIN should not be used once weekly in the continuation phase regimen in combination with isoniazid (INH) in HIV-infected patients with active pulmonary tuberculosis because of a higher rate of failure and/or relapse with rifampin (RIF)-resistant organisms [see Warnings and Precautions (5.4) and Clinical Studies (14.1)].

PRIFTIN has not been studied as part of the initial phase treatment regimen in HIV-infected patients with active pulmonary tuberculosis.

1.2 Latent Tuberculosis Infection

PRIFTIN is indicated in adults and pediatric patients 2 years and older for the treatment of latent tuberculosis infection caused by Mycobacterium tuberculosis in patients at high risk of progression to tuberculosis disease (including those in close contact with active tuberculosis patients, recent conversion to a positive tuberculin skin test, HIV-infected patients, or those with pulmonary fibrosis on radiograph) [see Clinical Studies (14.2)].

Limitations of Use

Active tuberculosis disease should be ruled out before initiating treatment for latent tuberculosis infection.

PRIFTIN must always be used in combination with isoniazid as a 12-week once-weekly regimen for the treatment of latent tuberculosis infection [see Dosage and Administration (2.2) and Clinical Studies (14.2)].

- PRIFTIN in combination with isoniazid is not recommended for individuals presumed to be exposed to rifamycin-resistant or isoniazid-resistant M. tuberculosis.

2 DOSAGE AND ADMINISTRATION

2.1 Dosage in Active Pulmonary Tuberculosis

PRIFTIN is only recommended for the treatment of active pulmonary tuberculosis caused by drug-susceptible organisms as part of regimens consisting of a 2-month initial phase followed by a 4-month continuation phase.

PRIFTIN should not be used in the treatment of active pulmonary tuberculosis caused by rifampin-resistant strains.

Initial phase (2 Months): PRIFTIN should be administered at a dose of 600 mg twice weekly for two months as directly observed therapy (DOT), with an interval of no less than 3 consecutive days (72 hours) between doses, in combination with other antituberculosis drugs as part of an appropriate regimen which includes daily companion drugs such as isoniazid (INH), ethambutol (EMB) and pyrazinamide (PZA).

Continuation phase (4 Months): Following the initial phase (2 months), continuation phase (4 months) treatment consists of PRIFTIN 600 mg once weekly for 4 months in combination with isoniazid or another appropriate antituberculosis agent for susceptible organisms administered as directly observed therapy.

2.2 Dosage in Latent Tuberculosis Infection

PRIFTIN should be administered once weekly in combination with isoniazid for 12 weeks as directly observed therapy.

Adults and pediatric patients 12 years and older: The recommended dose of PRIFTIN should be determined based on weight of the patient up to a maximum of 900 mg once weekly (see Table 1). The recommended dose of isoniazid is 15 mg/kg (rounded to the nearest 50 mg or 100 mg) up to a maximum of 900 mg once weekly for 12 weeks.

Pediatric Patients 2 to 11 years: The recommended dose of PRIFTIN should be determined based on weight of the patient up to a maximum of 900 mg once weekly (see Table 1). The recommended dose of isoniazid is 25 mg/kg (rounded to the nearest 50 mg or 100 mg) up to a maximum of 900 mg once weekly for 12 weeks.

Table 1: Weight Based Dose of PRIFTIN in the Treatment of Latent Tuberculosis Infection
Weight range | PRIFTIN dose | Number of PRIFTIN tablets
10–14 kg | 300 mg | 2
14.1–25 kg | 450 mg | 3
25.1–32 kg | 600 mg | 4
32.1–50 kg | 750 mg | 5
>50 kg | 900 mg | 6

2.3 Administration

Take PRIFTIN with meals. Administration of PRIFTIN with a meal increases oral bioavailability and may reduce the incidence of gastrointestinal upset, nausea, and/or vomiting [see Clinical Pharmacology (12.3)].

For patients who cannot swallow tablets, the tablets may be crushed and added to a small amount of semi-solid food, all of which should be consumed immediately [see Clinical Pharmacology (12.3)].

3 DOSAGE FORMS AND STRENGTHS

PRIFTIN is supplied as 150 mg round normal convex dark-pink film-coated tablets debossed "F" on one side of tablet.

4 CONTRAINDICATIONS

4.1 Hypersensitivity

PRIFTIN is contraindicated in patients with a history of hypersensitivity to rifamycins.

5 WARNINGS AND PRECAUTIONS

5.1 Hepatotoxicity

Elevations of liver transaminases may occur in patients receiving PRIFTIN [see Adverse Reactions (6.1)]. Patients on PRIFTIN should be monitored for symptoms of liver injury.

Patients with abnormal liver tests and/or liver disease or patients initiating treatment for active pulmonary tuberculosis should only be given PRIFTIN in cases of necessity and under strict medical supervision. In such patients, obtain serum transaminase levels prior to therapy and every 2 to 4 weeks while on therapy. Discontinue PRIFTIN if evidence of liver injury occurs.

5.2 Hypersensitivity and Related Reactions

Hypersensitivity reactions may occur in patients receiving PRIFTIN. Signs and symptoms of these reactions may include hypotension, urticaria, angioedema, acute bronchospasm, conjunctivitis, thrombocytopenia, neutropenia or flu-like syndrome (weakness, fatigue, muscle pain, nausea, vomiting, headache, fever, chills, aches, rash, itching, sweats, dizziness, shortness of breath, chest pain, cough, syncope, palpitations). There have been reports of anaphylaxis [see Patient Counseling Information (17)].

Monitor patients receiving PRIFTIN therapy for signs and/or symptoms of hypersensitivity reactions. If these symptoms occur, administer supportive measures and discontinue PRIFTIN.

5.3 Severe Cutaneous Adverse Reactions

Severe cutaneous adverse reactions (SCARs) such as Stevens-Johnson syndrome (SJS) and drug reaction with eosinophilia and systemic symptoms (DRESS) syndrome have been reported in association with the use of rifapentine (PRIFTIN) treatment regimens in patients with active and latent tuberculosis. Discontinue PRIFTIN at the first appearance of skin rash, mucosal lesions, or any other sign of hypersensitivity [see Patient Counseling Information (17)].

5.4 Relapse in the Treatment of Active Pulmonary Tuberculosis

PRIFTIN has not been evaluated as part of the initial phase treatment regimen in HIV-infected patients with active pulmonary TB.

Do not use PRIFTIN as a once-weekly continuation phase regimen in HIV-infected patients with active pulmonary tuberculosis because of a higher rate of failure and/or relapse with rifampin-resistant organisms [see Clinical Studies (14.1)].

Higher relapse rates may occur in patients with cavitary pulmonary lesions and/or positive sputum cultures after the initial phase of active tuberculosis treatment and in patients with evidence of bilateral pulmonary disease. Monitor for signs and symptoms of TB relapse in these patients [see Clinical Studies (14.1)].

Poor adherence to therapy is associated with high relapse rate. Emphasize the importance of compliance with therapy [see Patient Counseling Information (17)].

5.5 Paradoxical Drug Reactions

Paradoxical drug reactions are characterized by the recurrence or appearance of new symptoms or physical and radiological signs in a patient who had previously shown improvement with appropriate antimycobacterial treatment, in the absence of disease relapse, poor treatment compliance, drug resistance, side effects of treatment, or secondary infection/diagnosis. Paradoxical drug reactions have been reported with antimycobacterial therapy, including PRIFTIN, within the first few weeks or months of initiation of tuberculosis therapy [see Adverse Reactions (6.2)].

Paradoxical drug reactions are often transient and should not be misinterpreted as failure to respond to treatment. If worsening of symptoms or signs occurs during antimycobacterial treatment, consider paradoxical drug reaction in the differential diagnosis, and monitor or treat accordingly.

Advise patients to seek medical advice immediately if their symptoms of tuberculosis worsen or reappear.

5.6 Drug Interactions

Rifapentine is an inducer of CYP450 enzymes. Concomitant use of rifapentine with other drugs metabolized by these enzymes, such as protease inhibitors, certain reverse transcriptase inhibitors, and hormonal contraception may cause a significant decrease in plasma concentrations and loss of therapeutic effect [see Drug Interactions (7.1, 7.2, 7.3, 7.4) and Clinical Pharmacology (12.3)].

5.7 Discoloration of Body Fluids

PRIFTIN may produce a red-orange discoloration of body tissues and/or fluids (e.g., skin, teeth, tongue, urine, feces, saliva, sputum, tears, sweat, and cerebrospinal fluid). Contact lenses or dentures may become permanently stained.

5.8 Clostridioides Difficile–Associated Diarrhea

Clostridioides difficile–associated diarrhea (CDAD) has been reported with the use of nearly all systemic antibacterial agents, including PRIFTIN, with severity ranging from mild diarrhea to fatal colitis. Treatment with antibacterial agents can alter the normal flora of the colon and may permit overgrowth of C. difficile.

C. difficile produces toxins A and B which contribute to the development of CDAD. Hypertoxin producing strains of C. difficile cause increased morbidity and mortality, as these infections can be refractory to antimicrobial therapy and may require colectomy. CDAD must be considered in all patients who present with diarrhea following antibacterial use. Careful medical history is necessary because CDAD has been reported to occur over two months after the administration of antibacterial agents.

If CDAD is suspected or confirmed, discontinue antibacterial use not directed against C. difficile if possible. Institute appropriate measures such as fluid and electrolyte management, protein supplementation, antibacterial treatment of C. difficile, and surgical evaluation as clinically indicated.

5.9 Porphyria

Porphyria has been reported in patients receiving rifampin, attributed to induction of delta amino levulinic acid synthetase. Because PRIFTIN may have similar enzyme induction properties, avoid the use of PRIFTIN in patients with porphyria.

6 ADVERSE REACTIONS

The following serious and otherwise important adverse drug reactions are discussed in greater detail in other sections of labeling:

- Hepatotoxicity [see Warnings and Precautions (5.1)]
- Hypersensitivity [see Contraindications (4.1) and Warnings and Precautions (5.2)]
- Severe Cutaneous Adverse Reactions [see Warnings and Precautions (5.3)]
- Paradoxical Drug Reactions [see Warnings and Precautions (5.5)]
- Discoloration of Body Fluids [see Warnings and Precautions (5.7)]
- Clostridioides Difficile–Associated Diarrhea [see Warnings and Precautions (5.8)]
- Porphyria [see Warnings and Precautions (5.9)]

6.1 Clinical Trials Experience

Because clinical trials are conducted under widely varying conditions, adverse reaction rates observed in the clinical trials of a drug cannot be directly compared to rates in the clinical trials of another drug and may not reflect the rates observed in practice.

Active Pulmonary Tuberculosis

PRIFTIN was studied in a randomized, open label, active-controlled trial of HIV-negative patients with active pulmonary tuberculosis. The population consisted primarily of male subjects with a mean age of 37 ± 11 years. In the initial 2-month phase of treatment, 361 patients received PRIFTIN 600 mg twice a week in combination with daily isoniazid, pyrazinamide, and ethambutol and 361 subjects received rifampin in combination with isoniazid, pyrazinamide and ethambutol all administered daily. Ethambutol was discontinued when drug susceptibly testing was known. During the 4-month continuation phase, 317 patients in the PRIFTIN group continued to receive PRIFTIN 600 mg dosed once weekly with isoniazid and 304 patients in the rifampin group received twice weekly rifampin and isoniazid. Both treatment groups received pyridoxine (Vitamin B6) over the 6-month treatment period.

Because PRIFTIN was administered as part of a combination regimen, the adverse reaction profile reflects the entire regimen.

Twenty-two deaths occurred in the study, eleven in the rifampin combination therapy group and eleven in the PRIFTIN combination therapy group. 18/361 (5%) rifampin combination therapy patients discontinued the study due to an adverse reaction compared to 11/361 (3%) PRIFTIN combination therapy patients. Three patients (two rifampin combination therapy patients and one PRIFTIN combination therapy patient) were discontinued in the initial phase due to hepatotoxicity. Concomitant medications for all three patients included isoniazid, pyrazinamide, ethambutol, and pyridoxine. All three recovered without sequelae.

Five patients had adverse reactions associated with PRIFTIN overdose. These reactions included hematuria, neutropenia, hyperglycemia, ALT increased, hyperuricemia, pruritus, and arthritis.

Table 2 presents selected treatment-emergent adverse reactions associated with the treatment regimens which occurred in at least 1% of patients during treatment and post treatment through the first three months of follow-up.

Table 2: Selected Treatment Emergent Adverse Reactions during Treatment of Active Pulmonary Tuberculosis and through Three Months Follow-up
 | Initial Phase [Initial phase consisted of therapy with either PRIFTIN twice weekly or rifampin daily combined with daily isoniazid, pyrazinamide, and ethambutol for 60 days.] |  | Continuation Phase [Continuation phase consisted of therapy with either PRIFTIN once weekly or rifampin twice weekly combined with daily isoniazid for 120 days.]
System Organ Class Adverse Reaction | PRIFTIN Combination (N=361) N (%) | Rifampin Combination (N=361) N (%) | PRIFTIN Combination (N=317) N (%) | Rifampin Combination (N=304) N (%)
Blood and lymphatics
Anemia | 41 (11.4) | 41 (11.4) | 5 (1.6) | 10 (3.3)
Lymphopenia | 38 (10.5) | 37 (10.2) | 10 (3.2) | 9 (3.0)
Neutropenia | 22 (6.1) | 21 (5.8) | 27 (8.5) | 24 (7.9)
Leukocytosis | 6 (1.7) | 13 (3.6) | 5 (1.6) | 2 (0.7)
Thrombocytosis | 20 (5.5) | 13 (3.6) | 1 (0.3) | 0 (0.0)
Thrombocytopenia | 6 (1.7) | 6 (1.7) | 4 (1.3) | 6 (2)
Lymphadenopathy | 4 (1.1) | 2 (0.6) | 0 (0.0) | 2 (0.7)
Eye
Conjunctivitis | 8 (2.2) | 2 (0.6) | 1 (0.3) | 1 (0.3)
Gastrointestinal
Dyspepsia | 6 (1.7) | 11 (3) | 4 (1.3) | 6 (2)
Vomiting | 6 (1.7) | 14 (3.9) | 3 (0.9) | 3 (1)
Nausea | 7 (1.9) | 3 (0.8) | 2 (0.6) | 1 (0.3)
Diarrhea | 5 (1.4) | 2 (0.6) | 2 (0.6) | 0 (0.0)
General
Back Pain | 15 (4.2) | 11 (3) | 11 (3.5) | 4 (1.3)
Abdominal Pain | 3 (0.8) | 3 (0.8) | 4 (1.3) | 4 (1.3)
Fever | 5 (1.4) | 7 (1.9) | 1 (0.3) | 1 (0.3)
Anorexia | 14 (3.9) | 18 (5) | 8 (2.5) | 6 (2)
Hepatic and biliary
ALT Increased | 18 (5) | 23 (6.4) | 7 (2.2) | 10 (3.3)
AST Increased | 15 (4.2) | 18 (5) | 7 (2.2) | 8 (2.6)
Investigations
Blood urea increased | 4 (1.1) | 3 (0.8) | 10 (3.2) | 15 (4.9)
Musculoskeletal
Arthralgia | 13 (3.6) | 13 (3.6) | 3 (0.9) | 5 (1.6)
Neurologic
Headache | 11 (3) | 13 (3.6) | 3 (0.9) | 7 (2.3)
Dizziness | 5 (1.4) | 5 (1.4) | 1 (0.3) | 1 (0.3)
Respiratory
Hemoptysis | 27 (7.5) | 20 (5.5) | 6 (1.9) | 6 (2)
Coughing | 21 (5.8) | 8 (2.2) | 9 (2.8) | 11 (3.6)
Skin
Rash | 15 (4.2) | 26 (7.2) | 8 (2.5) | 8 (2.6)
Sweating Increased | 19 (5.3) | 18 (5) | 5 (1.6) | 4 (1.3)
Pruritus | 10 (2.8) | 16 (4.4) | 3 (0.9) | 0 (0.0)
Rash Maculopapular | 6 (1.7) | 3 (0.8) | 0 (0.0) | 1 (0.3)

The following selected treatment-emergent adverse reactions were reported in less than 1% of the PRIFTIN combination therapy patients during treatment and post treatment through the first three months of follow-up.

Blood and Lymphatics: lymphocytosis, hematoma, purpura, thrombosis.

Cardiovascular: syncope, tachycardia, palpitation, orthostatic hypotension, pericarditis.

Metabolic & Nutritional: alkaline phosphatase increased.

Gastrointestinal: gastritis, esophagitis, pancreatitis, salivary gland enlargement.

General: asthenia, facial edema.

Hepatobiliary: bilirubinemia, hepatomegaly, jaundice.

Infectious Disease: infection fungal.

Musculoskeletal: myalgia, myositis.

Neurologic: somnolence, dysphonia.

Pregnancy, Puerperium and Perinatal Conditions: abortion.

Psychiatric: anxiety, confusion.

Reproductive Disorders: vaginitis, vaginal hemorrhage, leukorrhea.

Respiratory: dyspnea, pneumonitis, pulmonary fibrosis, asthma, bronchospasm, laryngeal edema, laryngitis.

Skin: urticaria, skin discoloration.

In another randomized, open-label trial, 1075 HIV non-infected and infected patients with active pulmonary tuberculosis who had completed an initial 2-month phase of treatment with 4 drugs were randomly assigned to receive either PRIFTIN 600 mg and isoniazid once weekly or rifampin and isoniazid twice weekly for the 4-month continuation phase. Five hundred and two non–HIV-infected and 36 HIV-infected patients were randomized to receive the PRIFTIN regimen and 502 HIV-noninfected and 35 HIV-infected patients were randomized to receive the rifampin regimen.

The death rate was 6.5% for the PRIFTIN combination regimen compared to 6.7% for the rifampin combination regimen.

Latent Tuberculosis Infection

Main study

PRIFTIN in combination with isoniazid given once weekly for 3 months (3RPT/INH) was compared to isoniazid given once daily for 9 months (9INH) in an open-label, randomized trial in patients with a positive tuberculin skin test, and at high risk for progression from latent tuberculosis infection to active tuberculosis disease. PRIFTIN was dosed by weight, and isoniazid mg/kg dose was determined according to age [see Dosage and Administration (2.2)] to a maximum of 900 mg each.

A total of 4040 patients received at least one dose of the 3RPT/INH regimen, including 348 pediatric patients 2 to 17 years of age and 105 HIV-infected individuals. A total of 3759 received at least one dose of the 9INH regimen, including 342 pediatric patients 2 to 17 years of age and 95 HIV-infected individuals.

Patients were followed for 33 months from the time of enrollment. Treatment-emergent adverse reactions were defined as those occurring during treatment and 60 days after the last dose of treatment. One hundred and sixty-one (4%) 3RPT/INH subjects had a rifamycin hypersensitivity reaction, defined as either: a) one of the following: hypotension, urticaria, angioedema, acute bronchospasm, or conjunctivitis occurring in relation to study drug or b) at least four of the following symptoms occurring in relation to the study drug, with at least one symptom being CTCAE Grade 2 or higher: weakness, fatigue, nausea, vomiting, headache, fever, aches, sweats, dizziness, shortness of breath, flushing or chills. No specific definition was used for isoniazid hypersensitivity; 18 (0.5%) 9INH subjects were classified as having a hypersensitivity reaction. Hepatotoxicity was defined as AST ≥3 × upper limit of normal in the presence of specific signs and symptoms of hepatitis, or AST >5 × upper limit of normal regardless of signs or symptoms. One hundred and thirteen (3%) 9INH subjects and 24 (0.6%) 3RPT/INH subjects developed hepatotoxicity.

One hundred and ninety-six subjects (4.9%) in the 3RPT/INH arm discontinued treatment due to a treatment related adverse reaction patients and 142 (3.8%) in the 9INH arm discontinued treatment due to a treatment related adverse reaction. In the 3RPT/INH group, the most frequent treatment related adverse reaction resulting in treatment discontinuation was hypersensitivity reaction, occurring in 120 (3%) patients. In the 9INH group, the most frequent treatment related adverse reaction resulting in treatment discontinuation was hepatotoxicity, occurring in 76 (2%) patients.

Seventy-one deaths occurred, 31/4040, 0.77% in the 3RPT/INH group and 40/3759 (1.06%) in the 9INH group) during the 33-month study period. During the treatment emergent period, 11 deaths occurred, 4 in the 3RPT/INH group and 7 in the 9INH group. None of the reported deaths were considered related to treatment with study drugs or were attributed to tuberculosis disease.

Table 3 presents select adverse reactions that occurred during the treatment emergent period in the main study in LTBI patients treated with 3RPT/INH or 9INH at a frequency greater than 0.5%.

Table 3: Select Adverse Reactions Occurring in 0.5% or Greater of Patients [Includes events reported through 60 days after last dose of study drug.] in the Latent Tuberculosis Infection Main Study
System Organ Class Adverse Reaction | 3RPT/INH (N=4040) N (%) | 9INH (N=3759) N (%)
Immune system disorders
Hypersensitivity | 161 (4) | 18 (0.5)
Hepatobiliary disorders
Hepatitis | 24 (0.6) | 113 (3)
Nervous system disorders
Headache | 26 (0.6) | 17 (0.5)
Skin and subcutaneous tissue disorders
Skin reaction | 31 (0.8) | 21 (0.6)

Pediatric substudy

Six hundred and ninety pediatric patients 2 to 17 years of age received at least one dose of study drugs in the main study. An additional 342 pediatric patients 2 to 17 years of age received at least one dose in the pediatric extension study (total 1032 pediatric patients; 539 received 3RPT/INH and 493 received 9INH).

No pediatric patients in either treatment arm developed hepatotoxicity. Using the same definition for rifamycin hypersensitivity reaction as in the main study, 7 (1.3%) of pediatric patients in the 3RPT/INH group experienced a rifamycin hypersensitivity reaction. Adverse reactions in pediatric patients 2 to 11 years of age and 12 to 17 years of age were similar.

HIV substudy

Two hundred HIV-infected patients with latent tuberculosis infection received at least one dose of study drugs in the main study and an additional 193 patients received at least one dose in the extension study (total of 393; 207 received 3RPT/INH and 186 received 9INH). Compared to the HIV-negative patients enrolled in the main study, a higher proportion of HIV-infected patients in each treatment arm experienced a treatment emergent adverse reaction, including a higher incidence of hepatotoxicity. Hepatotoxicity occurred in 3/207 (1.5%) patients in the 3RPT/INH arm and in 14/186 (7.5%) in the 9INH arm. Rifamycin hypersensitivity occurred in only one HIV-infected patient.

Eleven deaths occurred during the 33-month follow up period (6/207 in the 3RPT/INH group and 5/186 in the 9INH group) including one death in the 9INH arm during the treatment emergent period. None of the reported deaths were considered related to treatment with study drugs or tuberculosis disease.

Selected treatment-emergent adverse reactions reported during treatment and 60 days post treatment in less than 0.5% of the 3RPT/INH combination-therapy group in the main study are presented below by body system.

Eye Disorders: conjunctivitis.

Blood and Lymphatic System Disorders: leukopenia, anemia, lymphadenopathy, neutropenia.

Gastrointestinal Disorders: nausea, diarrhea, vomiting, abdominal pain, constipation, dry mouth, dyspepsia, esophageal irritation, gastritis, pancreatitis.

General Disorders and Administration Site Conditions: fatigue, pyrexia, asthenia, chest pain, chills, feeling jittery.

Infections and Infestations: pharyngitis, viral infection, vulvovaginal candidiasis.

Metabolism and Nutrition Disorders: hyperglycemia, gout, hyperkalemia, decreased appetite, hyperlipidemia.

Musculoskeletal and Connective Tissue Disorders: arthralgia, myalgia, back pain, rhabdomyolysis.

Nervous System Disorders: dizziness, convulsion, paresthesia, headache, neuropathy peripheral, syncope.

Psychiatric Disorders: depression, anxiety, disorientation, suicidal ideation.

Renal and Urinary Disorders: azotemia.

Reproductive System and Breast Disorders: vulvovaginal pruritus.

Respiratory, Thoracic and Mediastinal Disorders: cough, dyspnea, oropharyngeal pain, asthma, bronchial hyperactivity, epistaxis.

Skin and Subcutaneous Tissue Disorders: rash, hyperhidrosis, pruritus, urticaria.

6.2 Postmarketing Experience

The following adverse reactions have been identified from postmarketing surveillance of rifapentine. Because these reactions are reported from a population of unknown size, it is not always possible to estimate their frequency or establish a causal relationship to drug exposure.

General and administration site conditions: Paradoxical drug reactions.

Skin and subcutaneous tissue disorders: Severe cutaneous adverse reactions (SCARs) such as Stevens-Johnson syndrome (SJS) and drug reaction with eosinophilia and systemic symptoms (DRESS) syndrome.

7 DRUG INTERACTIONS

7.1 Protease Inhibitors and Reverse Transcriptase Inhibitors

Rifapentine is an inducer of CYP450 enzymes. Concomitant use of PRIFTIN with other drugs metabolized by these enzymes, such as protease inhibitors and certain reverse transcriptase inhibitors, may cause a significant decrease in plasma concentrations and loss of therapeutic effect of the protease inhibitor or reverse transcriptase inhibitor [see Warnings and Precautions (5.6) and Clinical Pharmacology (12.3)].

7.2 Fixed-Dose Combination of Efavirenz, Emtricitabine, and Tenofovir

Once-weekly coadministration of 900 mg PRIFTIN with the antiretroviral fixed-dose combination of efavirenz 600 mg, emtricitabine 200 mg and tenofovir disoproxil fumarate 300 mg in HIV-infected patients did not result in any substantial change in steady state exposures of efavirenz, emtricitabine, and tenofovir. No clinically significant change in CD4 cell counts or viral loads were noted [see Clinical Pharmacology (12.3)].

7.3 Hormonal Contraceptives

PRIFTIN may reduce the effectiveness of hormonal contraceptives. Patients using hormonal contraception should be advised to use an alternative non-hormonal contraceptive method or add a barrier method of contraception during treatment with PRIFTIN [see Use in Specific Populations (8.3) and Clinical Pharmacology (12.3)].

7.4 Cytochrome P450 3A4 and 2C8/9

Rifapentine is an inducer of cytochromes P450 3A4 and P450 2C8/9. Therefore, PRIFTIN may increase the metabolism of other coadministered drugs that are metabolized by these enzymes. Induction of enzyme activities by PRIFTIN occurred within 4 days after the first dose. Enzyme activities returned to baseline levels 14 days after discontinuing PRIFTIN.

Rifampin has been reported to accelerate the metabolism and may reduce the activity of the following drugs; hence, PRIFTIN may also increase the metabolism and decrease the activity of these drugs. Dosage adjustments of the drugs in Table 4 or of other drugs metabolized by cytochrome P450 3A4 or P450 2C8/9 may be necessary if they are given concurrently with PRIFTIN.

Table 4: Drug Interactions with PRIFTIN: Dosage Adjustment May be Necessary
Drug Class | Examples of Drugs Within Class
Antiarrhythmics | Disopyramide, mexiletine, quinidine, tocainide
Antibiotics | Chloramphenicol, clarithromycin, dapsone, doxycycline; Fluoroquinolones (such as ciprofloxacin)
Oral Anticoagulants | Warfarin
Anticonvulsants | Phenytoin
Antimalarials | Quinine
Azole Antifungals | Fluconazole, itraconazole, ketoconazole
Antipsychotics | Haloperidol
Barbiturates | Phenobarbital
Benzodiazepines | Diazepam
Beta-Blockers | Propranolol
Calcium Channel Blockers | Diltiazem, nifedipine, verapamil
Cardiac Glycoside Preparations | Digoxin
Corticosteroids | Prednisone
Fibrates | Clofibrate
Oral Hypoglycemics | Sulfonylureas (e.g., glyburide, glipizide)
Hormonal Contraceptives/Progestins | Ethinyl estradiol, levonorgestrel
Immunosuppressants | Cyclosporine, tacrolimus
Methylxanthines | Theophylline
Narcotic analgesics | Methadone
Phosphodiesterase-5 (PDE-5) Inhibitors | Sildenafil
Thyroid preparations | Levothyroxine
Tricyclic antidepressants | Amitriptyline, nortriptyline

7.5 Other Interactions

The conversion of PRIFTIN to 25-desacetyl rifapentine is mediated by an esterase enzyme. There is minimal potential for PRIFTIN metabolism to be inhibited or induced by another drug, based upon the characteristics of the esterase enzymes.

Since PRIFTIN is highly bound to albumin, drug displacement interactions may also occur [see Clinical Pharmacology (12.3)].

7.6 Interactions with Laboratory Tests

Therapeutic concentrations of rifampin have been shown to inhibit standard microbiological assays for serum folate and Vitamin B12. Similar drug-laboratory interactions should be considered for PRIFTIN; thus, alternative assay methods should be considered.

8 USE IN SPECIFIC POPULATIONS

8.1 Pregnancy

Risk Summary

Based on animal data, PRIFTIN may cause fetal harm when administered to a pregnant woman. Available data from clinical trials, case reports, epidemiology studies and postmarketing experience with PRIFTIN use in pregnant women are insufficient to establish a drug-associated risk of major birth defects, adverse maternal or fetal outcomes. In two clinical trials, a total of 59 patients who were treated with rifapentine in combination with other anti-tuberculosis drugs became pregnant. Overall, the reported rate of miscarriage following rifapentine exposure in these two clinical trials did not represent an increase over the background rate of miscarriage reported in the general population (see Data). There are risks associated with active tuberculosis during pregnancy. When administered during the last few weeks of pregnancy, PRIFTIN may be associated with maternal postpartum hemorrhage and bleeding in the exposed neonates (see Clinical Considerations). In animal reproduction and developmental toxicity studies, adverse developmental outcomes (including cleft palate or mal-positioned aortic arches) were observed following administration of rifapentine to pregnant rats and rabbits at doses approximately 0.6 and 0.3 to 1.3 times, respectively, of the recommended human dose based on body surface area comparisons (see Data). Based on animal data, advise pregnant women of the risk for fetal harm. As rifapentine is always used in combination with other antituberculosis drugs such as isoniazid, ethambutol, and pyrazinamide, refer to the prescribing information of the other drug(s) for more information on their associated risks of use during pregnancy.

The estimated background risk of major birth defects and miscarriage for the indicated population is unknown. All pregnancies have a background risk of birth defect, loss, or other adverse outcomes. In the U.S. general population, the estimated background risk of major birth defects and miscarriage in clinically recognized pregnancies is 2%–4% and 15%–20%, respectively.

Clinical Considerations

Disease-associated maternal and/or embryo-fetal risk

Active tuberculosis in pregnancy is associated with adverse maternal and neonatal outcomes including maternal anemia, cesarean delivery, preterm birth, low birth weight, birth asphyxia, and perinatal infant death.

Labor or delivery

When administered during the last few weeks of pregnancy, PRIFTIN may increase the risk for maternal postpartum hemorrhage and bleeding in the exposed neonate. Monitor prothrombin time of pregnant women and neonates who are exposed to PRIFTIN during the last few weeks of pregnancy. Treatment with Vitamin K may be indicated.

Data

Human data

Fourteen patients with active tuberculosis treated with multiple antituberculosis drugs including PRIFTIN became pregnant during clinical studies. Six delivered normal infants, four had first trimester spontaneous abortions (of these, one patient abused ethanol and another patient was HIV-infected), one had an elective abortion, and outcome was unknown in three patients. These data are, however, limited by the quality of reporting and confounded by comorbid medical conditions and multiple antituberculosis drug exposures.

In the trial that compared the safety and effectiveness of PRIFTIN in combination with isoniazid to isoniazid alone for the treatment of latent tuberculosis infection, a total of 45 (2.5%) women in the PRIFTIN/isoniazid arm and 71 (4.1%) women in the isoniazid arm became pregnant. Among the 46 total pregnancies in the PRIFTIN/isoniazid arm, there were 31 live births, 6 elective abortions, 7 spontaneous abortions, and 2 unknown outcomes. Of the 31 live infants, 21 were reported healthy while in the other ten cases no further details were available. The rate of spontaneous abortion in the PRIFTIN/isoniazid arm (15%) and the rate of spontaneous abortion in the isoniazid arm (19%) did not represent an increase over the background rate of 15 to 20 percent reported in the general population. Further interpretation of these results is limited by the quality of adverse event reporting.

Animal data

Animal studies in rats and rabbits revealed malformations and other adverse developmental outcomes in both species. Pregnant rats given oral rifapentine during organogenesis (gestational days 5 through 15) at 40 mg/kg/day (0.6 times the human dose of 600 mg based on body surface area comparisons) produced pups with cleft palates and mal-positioned aortic arches, delayed ossification, increased number of ribs, a decrease in litter size and mean litter weight, an increase in number of stillbirths, and an increase in mortality during lactation.

When rifapentine was administered orally to mated female rats late in gestation, at 20 mg/kg/day (0.3 times the human dose based on body surface area), pup weights and gestational survival (live pups born/pups born) were reduced compared to controls. Increased resorptions and postimplantation loss, decreased mean fetal weights, increased numbers of stillborn pups, and slightly increased pup mortality during lactation were also noted. When pregnant rabbits received oral rifapentine at 10 mg/kg to 40 mg/kg (0.3 times to 1.3 times the human dose based on body surface area) during organogenesis (GD6 to GD18), major fetal malformations occurred including: ovarian agenesis, pes varus, arhinia, microphthalmia, and irregularities of the ossified facial tissues. At 40 mg/kg/day, there were increases in postimplantation loss and the incidence of stillborn pups.

8.2 Lactation

Risk Summary

There are no data on the presence of rifapentine or its metabolite in human or animal milk, the effects on the breastfed infant, or the effects on milk production. Since PRIFTIN may produce a red-orange discoloration of body fluids, there is a potential for discoloration of breast milk. Monitor infants exposed to rifapentine through breast milk for signs of hepatotoxicity (see Clinical Considerations). The developmental and health benefits of breastfeeding should be considered along with the mother's clinical need for PRIFTIN and any potential adverse effects on the breastfed infant from PRIFTIN or from the underlying maternal condition.

Clinical Considerations

Monitor infants exposed to rifapentine through breast milk for signs of hepatotoxicity to include irritability, prolonged unexplained crying, yellowing of the eyes, loss of appetite, vomiting, and changes in color of the urine (darkening) or stool (lightening, pale or light brown).

8.3 Females and Males of Reproductive Potential

Contraception

Use of PRIFTIN may reduce the efficacy of hormonal contraceptives. Advise patients using hormonal contraceptives to use an alternative non-hormonal contraceptive method or add a barrier method of contraception during treatment with PRIFTIN [see Warnings and Precautions (5.6) and Drug Interactions (7.3)].

8.4 Pediatric Use

The safety and effectiveness of PRIFTIN in the treatment of active pulmonary tuberculosis have not been established in pediatric patients under the age of 12.

The safety and effectiveness of PRIFTIN in combination with isoniazid once-weekly regimen has been evaluated in pediatric patients (2 to 17 years of age) for the treatment of latent tuberculosis infection. In clinical studies, the safety profile in pediatric patients was similar to that observed in adult patients [see Adverse Reactions (6.1) and Clinical Studies (14.2)].

In a pharmacokinetic study conducted in 2 to 11-year-old pediatric patients with latent tuberculosis infection, PRIFTIN was administered once weekly based on weight (15 mg/kg to 30 mg/kg, up to a maximum of 900 mg). Exposures (AUC) in pediatric patients 2 to 11 years old with latent tuberculosis infection were higher (average 31%) than those observed in adults receiving PRIFTIN 900 mg once weekly [see Dosage and Administration (2.2) and Clinical Pharmacology (12.3)].

8.5 Geriatric Use

Clinical studies with PRIFTIN did not include sufficient numbers of subjects aged 65 years and over to determine whether they respond differently from younger subjects. In a pharmacokinetic study with PRIFTIN, no substantial differences in the pharmacokinetics of rifapentine and 25-desacetyl metabolite were observed in the elderly compared to younger adults [see Clinical Pharmacology (12.3)].

10 OVERDOSAGE

While there is no experience with the treatment of acute overdose with PRIFTIN, clinical experience with rifamycins suggests that gastric lavage to evacuate gastric contents (within a few hours of overdose), followed by instillation of an activated charcoal slurry into the stomach, may help adsorb any remaining drug from the gastrointestinal tract.

Rifapentine and 25-desacetyl rifapentine are 97.7% and 93.2% plasma protein bound, respectively. Rifapentine and related compounds excreted in urine account for only 17% of the administered dose, therefore, neither hemodialysis nor forced diuresis is expected to enhance the systemic elimination of unchanged rifapentine from the body of a patient with PRIFTIN overdose.

11 DESCRIPTION

PRIFTIN (rifapentine) for oral administration contains 150 mg of the active ingredient rifapentine per tablet.

The 150 mg tablets also contain, as inactive ingredients: calcium stearate, disodium EDTA, FD&C Blue No. 2 aluminum lake, hydroxypropyl cellulose, hypromellose USP, microcrystalline cellulose, polyethylene glycol, pregelatinized starch, propylene glycol, sodium ascorbate, sodium lauryl sulfate, sodium starch glycolate, synthetic red iron oxide, and titanium dioxide.

Rifapentine is a rifamycin derivative antimicrobial and has a similar profile of microbiological activity to rifampicin. The molecular weight is 877.04.

The molecular formula is C47H64N4O12.

The chemical name for rifapentine is rifamycin, 3-[[(4-cyclopentyl-1-piperazinyl)imino]methyl]- or 3-[N-(4-cyclopentyl - 1-piperazinyl)formimidoyl] rifamycin or 5,6,9,17,19,21-hexahydroxy-23-methoxy-2,4,12,16,18,20,22-heptamethyl-8-[N-(4-cyclopentyl-l-piperazinyl)-formimidoyl]-2,7-(epoxypentadeca[1,11,13]trienimino)naphtho[2,1-b]furan-1,11(2H)-dione 21-acetate. It has the following structure:

12 CLINICAL PHARMACOLOGY

12.1 Mechanism of Action

Rifapentine, a cyclopentyl rifamycin, is an antimycobacterial agent [see Microbiology (12.4)].

12.3 Pharmacokinetics

When oral doses of PRIFTIN were administered once daily or once every 72 hours to healthy volunteers for 10 days, single dose AUC (0–∞) of rifapentine was similar to its steady-state AUCss (0–24h) or AUCss (0–72h) values, suggesting no significant auto-induction effect on steady-state pharmacokinetics of rifapentine. Steady-state conditions were achieved by day 10 following daily administration of PRIFTIN 600 mg. No plasma accumulation of rifapentine and 25-desacetyl rifapentine (active metabolite) is expected after once weekly administration of PRIFTIN.

The pharmacokinetic parameters of rifapentine and 25-desacetyl rifapentine on day 10 following oral administration of 600 mg PRIFTIN every 72 hours to healthy volunteers are described in Table 5.

Table 5: Pharmacokinetics and Rifapentine and 25-Desacetyl Rifapentine in Healthy Volunteers
Parameter | Rifapentine | 25-desacetyl Rifapentine
Parameter | Mean ± SD (n=12)
Cmax (µg/mL) | 15.05 ± 4.62 | 6.26 ± 2.06
AUC (0–72h) (µg∙h/mL) | 319.54 ± 91.52 | 215.88 ± 85.96
T1/2 (h) | 13.19 ± 1.38 | 13.35 ± 2.67
Tmax (h) | 4.83 ± 1.80 | 11.25 ± 2.73
Cl/F (L/h) | 2.03 ± 0.60 | --

The pharmacokinetic parameters of rifapentine and 25-desacetyl rifapentine following single-dose oral administration of 900 mg PRIFTIN in combination with 900 mg isoniazid in fed conditions are described in Table 6.

Table 6: Mean ± SD Pharmacokinetic Parameters of Rifapentine and 25-Desacetyl Rifapentine in Healthy Volunteers When PRIFTIN is Coadministered with Isoniazid Under Fed Conditions (N=16)
Parameter | Rifapentine | 25-desacetyl Rifapentine
Cmax (µg/mL) | 25.8 ± 5.83 | 13.3 ± 4.83
AUC (µg∙h/mL) | 817 ± 128 | 601 ± 187
T1/2(h) | 16.6 ± 5.02 | 17.5 ± 7.42
Tmax (h) [Median (Min–Max).] | 8 (3–10) | 24 (10–36)
Cl/F (L/h) | 1.13 ± 0.174 | NA [Not Applicable.]

Absorption

The absolute bioavailability of PRIFTIN has not been determined. The relative bioavailability (with an oral solution as a reference) of PRIFTIN after a single 600 mg dose to healthy adult volunteers was 70%. The maximum concentrations were achieved from 5 hours to 6 hours after administration of the 600 mg PRIFTIN dose.

The administration of PRIFTIN with a high fat meal increased rifapentine Cmax and AUC by 40% to 50% over that observed when PRIFTIN was administered under fasting conditions.

The administration of PRIFTIN (900 mg single dose) and isoniazid (900 mg single dose) with a low fat, high carbohydrate breakfast, led to a 47% and 51% increase in rifapentine Cmax and AUC, respectively. In contrast, the ingestion of the same meal decreased isoniazid Cmax and AUC by 46% and of 23%, respectively.

Distribution

In a population pharmacokinetic analysis in 351 tuberculosis patients who received 600 mg PRIFTIN in combination with isoniazid, pyrazinamide and ethambutol, the estimated apparent volume of distribution was 70.2 ± 9.1 L. In healthy volunteers, rifapentine and 25-desacetyl rifapentine were 97.7% and 93.2% bound to plasma proteins, respectively. Rifapentine was mainly bound to albumin. Similar extent of protein binding was observed in healthy volunteers, asymptomatic HIV-infected subjects and hepatically impaired subjects.

Metabolism/Excretion

Following a single 600 mg oral dose of radiolabeled rifapentine to healthy volunteers (n=4), 87% of the total ^14C-rifapentine was recovered in the urine (17%) and feces (70%). Greater than 80% of the total ^14C-rifapentine dose was excreted from the body within 7 days. Rifapentine was hydrolyzed by an esterase enzyme to form a microbiologically active 25-desacetyl rifapentine. Rifapentine and 25-desacetyl rifapentine accounted for 99% of the total radioactivity in plasma. Plasma AUC(0–∞) and Cmax values of the 25-desacetyl rifapentine metabolite were one-half and one-third those of the rifapentine, respectively. Based upon relative in vitro activities and AUC(0– ∞) values, rifapentine and 25-desacetyl rifapentine potentially contributes 62% and 38% to the clinical activities against M. tuberculosis, respectively.

Specific Populations

Gender: In a population pharmacokinetics analysis of sparse blood samples obtained from 351 tuberculosis patients who received 600 mg PRIFTIN in combination with isoniazid, pyrazinamide and ethambutol, the estimated apparent oral clearance of PRIFTIN for males and females was 2.51 ± 0.14 L/h and 1.69 ± 0.41 L/h, respectively. The clinical significance of the difference in the estimated apparent oral clearance is not known.

Elderly: Following oral administration of a single 600 mg dose of PRIFTIN to elderly (65 years and older) male healthy volunteers (n=14), the pharmacokinetics of rifapentine and 25-desacetyl metabolite were similar to that observed for young (18 to 45 years) healthy male volunteers (n=20).

Pediatric: In a pharmacokinetic study in pediatric patients (age 2 to 12 years), a single oral dose of 150 mg PRIFTIN was administered to those weighing less than 30 kg (n=11) and a single oral dose of 300 mg was administered to those weighing greater than 30 kg (n=12). The mean estimates of AUC and Cmax were approximately 30% to 50% lower in these pediatric patients than those observed in healthy adults administered single oral doses of 600 mg and 900 mg.

A study compared the pharmacokinetics of rifapentine in pediatric patients (age 2 years to 11 years) with latent tuberculosis infection (n=80) receiving PRIFTIN once weekly based on weight (15 mg/kg to 30 mg/kg, up to a maximum of 900 mg, see Table 1) to that of adults (n=77) receiving PRIFTIN 900 mg once weekly. Pediatric patients who could not swallow whole tablets were administered crushed tablets mixed in soft food. Overall, the geometric mean AUC of rifapentine in this age group was 31% higher compared to adult patients receiving 900 mg PRIFTIN once weekly (720 versus 551 mcg∙h/mL). The geometric mean AUC of rifapentine was 60% higher in pediatric patients administered whole tablets (884 versus 551 mcg∙h/mL) and 19% higher in pediatric patients administered crushed tablets (656 versus 551 mcg∙h/mL), as compared to exposures in adults. Pediatric patients administered crushed PRIFTIN tablets had 26% lower rifapentine exposures compared to those pediatric patients who were given whole tablets.

Population pharmacokinetic analysis showed that rifapentine clearance adjusted to body weight decreased with increasing age of pediatric patients (2 to 18 years).

In another pharmacokinetics study of PRIFTIN in healthy adolescents (age 12 to 15 years), 600 mg PRIFTIN was administered to those weighing ≥45 kg (n=10) and 450 mg was administered to those weighing less than 45 kg (n=2). The pharmacokinetics of rifapentine was similar to those observed in healthy adults.

Renal Impaired Patients: The pharmacokinetics of rifapentine has not been evaluated in renal impaired patients. Although only about 17% of an administered dose is excreted via the kidneys, the clinical significance of impaired renal function on the disposition of rifapentine and its 25-desacetyl metabolite is not known.

Hepatic Impaired Patients: Following oral administration of a single 600 mg dose of PRIFTIN to mild to severe hepatic impaired patients (n=15), the pharmacokinetics of rifapentine and 25-desacetyl metabolite were similar in patients with various degrees of hepatic impairment and to that observed in another study for healthy volunteers (n=12).

Asymptomatic HIV-Infected Volunteers: Following oral administration of a single 600 mg dose of PRIFTIN to asymptomatic HIV-infected volunteers (n=15) under fasting conditions, mean Cmax and AUC(0–∞) of rifapentine were lower (20%–32%) than that observed in other studies in healthy volunteers (n=55). In a cross-study comparison, mean Cmax and AUC values of the 25-desacetyl rifapentine, when compared to healthy volunteers were higher (6%–21%) in one study (n=20), but lower (15%–16%) in a different study (n=40). The clinical significance of this observation is not known. Food (850 total calories: 33 g protein, 55 g fat, and 58 g carbohydrate) increases the mean AUC and Cmax of rifapentine observed under fasting conditions in asymptomatic HIV-infected volunteers by about 51% and 53%, respectively.

Drug-Drug Interactions

Isoniazid: Coadministration of PRIFTIN (900 mg single dose) and isoniazid (900 mg single dose), in fasted condition, did not result in any significant change in the exposure of rifapentine and isoniazid compared to when administered alone in fasted condition.

Rifapentine is an inducer of cytochrome P450 3A4 and 2C8/9. Therefore, it may increase the metabolism and decrease the activity of other coadministered drugs that are metabolized by these enzymes. Dosage adjustments of the coadministered drugs may be necessary if they are given concurrently with PRIFTIN [see Drug Interactions (7.4)].

Indinavir: In a study in which 600 mg PRIFTIN was administered twice weekly for 14 days followed by PRIFTIN twice weekly plus 800 mg indinavir 3 times a day for an additional 14 days, indinavir Cmax decreased by 55% while AUC reduced by 70%. Clearance of indinavir increased by 3-fold in the presence of PRIFTIN while half-life did not change. But when indinavir was administered for 14 days followed by coadministration with PRIFTIN for an additional 14 days, indinavir did not affect the pharmacokinetics of rifapentine [see Warnings and Precautions (5.6) and Drug Interactions (7.1)].

Fixed-dose combination of efavirenz, emtricitabine and tenofovir: Once-weekly coadministration of 900 mg PRIFTIN with the antiretroviral fixed-dose combination of efavirenz 600 mg, emtricitabine 200 mg and tenofovir disoproxil fumarate 300 mg in HIV-infected patients did not result in any substantial change in steady state exposures of efavirenz, emtricitabine, and tenofovir (Table 7). A 15% decrease in efavirenz Cmin and AUC and a 13% decrease in tenofovir Cmin were observed with repeated weekly doses of PRIFTIN (Table 7). No clinically significant change in CD4 cell counts or viral loads were noted.

Table 7: Treatment Ratio Estimates (with versus without repeated once-weekly PRIFTIN 900 mg) with 90% Confidence Intervals for Efavirenz, Emtricitabine and Tenofovir Pharmacokinetic Parameters
 | Efavirenz Point Estimates (90% CI) | Emtricitabine Point Estimates (90% CI) | Tenofovir Point Estimates (90% CI)
Cmax | 0.92 (0.82–1.03) | 0.95 (0.81–1.10) | 1.00 (0.82–1.22)
Cmin | 0.85 (0.79–0.93) | 0.97 (0.90–1.05) | 0.87(0.73–1.05)
AUC0–24 | 0.86 (0.79–0.93) | 0.93 (0.89–0.98) | 0.91(0.85–0.98)

12.4 Microbiology

Mechanism of Action

Rifapentine, a cyclopentyl rifamycin, inhibits DNA-dependent RNA polymerase in susceptible strains of Mycobacterium tuberculosis but does not affect mammalian cells at concentrations that are active against these bacteria. At therapeutic levels, rifapentine inhibits RNA transcription by preventing the initiation of RNA chain formation. It forms a stable complex with bacterial DNA-dependent RNA polymerase, leading to repression of RNA synthesis and cell death. Rifapentine and its 25-desacetyl metabolite accumulate in human monocyte-derived macrophages and are bactericidal to both intracellular and extracellular M. tuberculosis bacilli.

Mechanism of Resistance

The mechanism of resistance to rifapentine appears to be similar to that of rifampin. Bacterial resistance to rifapentine is caused by an alteration in the target site, the beta subunit of the DNA-dependent RNA polymerase, caused by a one-step mutation in the rpoβgene. The incidence of rifapentine resistant mutants in an otherwise susceptible population of M. tuberculosis strains is approximately one in 10^7 to 10^8 bacilli. Rifapentine resistance appears to be associated with monotherapy. Therefore, rifapentine should always be used in combination with other antituberculosis drugs.

Cross Resistance

M. tuberculosis organisms resistant to other rifamycins are likely to be resistant to rifapentine. A high level of cross-resistance between rifamycin and rifapentine has been demonstrated with M. tuberculosis strains. Cross-resistance between rifapentine and non-rifamycin antimycobacterial agents has not been identified in clinical isolates.

Susceptibility Testing

For specific information regarding susceptibility test interpretive criteria and associated test methods and quality control standards recognized by FDA for this drug, please see: https://www.fda.gov/STIC.

13 NONCLINICAL TOXICOLOGY

13.1 Carcinogenesis, Mutagenesis, Impairment of Fertility

Hepatocellular carcinomas were increased in male NMRI mice (Harlan Winklemann) which were treated orally with rifapentine for two years at or above doses of 5 mg/kg/day (0.04 times the recommended human dose based on body surface area conversions). In a two year rat study, there was an increase in nasal cavity adenomas in Wistar rats treated orally with rifapentine at 40 mg/kg/day (0.6 times human dose based on body surface area conversions).

Rifapentine was negative in the following genotoxicity tests: in vitro gene mutation assay in bacteria (Ames test); in vitro point mutation test in Aspergillus nidulans; in vitro gene conversion assay in Saccharomyces cerevisiae; host-mediated (mouse) gene conversion assay with Saccharomyces cerevisiae; in vitro Chinese hamster ovary cell/hypoxanthine-guanine phosphoribosyltransferase (CHO/HGPRT) forward mutation assay; in vitro chromosomal aberration assay utilizing rat lymphocytes; and in vivo mouse bone marrow micronucleus assay.

The 25-desacetyl metabolite of rifapentine was positive in the in vitro mammalian chromosome aberration test in V79 Chinese hamster cells, but was negative in the in vitro gene mutation assay in bacteria (Ames test), the in vitro Chinese hamster ovary cell/hypoxanthine-guanine phosphoribosyltransferase (CHO/HGPRT) forward mutation assay, and the in vivo mouse bone marrow micronucleus assay. Fertility and reproductive performance were not affected by oral administration of rifapentine to male and female rats at doses of up to 20 mg/kg/day (one-third of the human dose based on body surface area conversions).

14 CLINICAL STUDIES

14.1 Active Pulmonary Tuberculosis

PRIFTIN was studied in two randomized, open-label controlled clinical trials in the treatment of active pulmonary tuberculosis.

The first trial was an open-label, prospective, parallel group, active-controlled trial in HIV-negative patients with active pulmonary tuberculosis. The population mostly comprised Black (approximately 60%) or multiracial (approximately 31%) patients. Treatment groups were comparable for age and sex and consisted primarily of male subjects with a mean age of 37 ± 11 years. In the initial 2-month phase of treatment, 361 patients received PRIFTIN 600 mg twice a week in combination with daily isoniazid, pyrazinamide, and ethambutol and 361 subjects received rifampin 600 mg in combination with isoniazid, pyrazinamide and ethambutol all administered daily. The doses of the companion drugs were the same in both treatment groups during the initial phase: isoniazid 300 mg, pyrazinamide 2000 mg, and ethambutol 1200 mg. For patients weighing less than 50 kg, the doses of rifampin (450 mg), pyrazinamide (1500 mg) and ethambutol (800 mg) were reduced. Ethambutol was discontinued when isoniazid and rifampin susceptibility testing results were confirmed. During the 4-month continuation phase, 317 patients in the PRIFTIN group continued to receive PRIFTIN 600 mg dosed once weekly with isoniazid 300 mg and 304 patients in the rifampin group received twice weekly rifampin and isoniazid 900 mg. For patients weighing less than 50 kg, the doses of rifampin (450 mg) and isoniazid (600 mg) were reduced. Both treatment groups received pyridoxine (Vitamin B6) over the 6-month treatment period. Treatment was directly observed. 65/361 (18%) of patients in the PRIFTIN group and 34/361 (9%) in the rifampin group received overdoses of one or more of the administered study medications during the initial or continuation phase of treatment. Seven of these patients had adverse reactions reported with the overdose (5 in the PRIFTIN group and 2 in the rifampin group).

Table 8 below contains assessments of sputum conversion at end of treatment (6 months) and relapse rates at the end of follow-up (24 months).

Table 8: Clinical Outcome in HIV Negative Patients with Active Pulmonary Tuberculosis (Trial 1)
 | PRIFTIN Combination Treatment % and (n/N [All data for patients with confirmed susceptible M. tuberculosis (PRIFTIN combination treatment, N=286; rifampin combination treatment, N=283).]) | Rifampin Combination Treatment % and (n/N)
Status at End of 6 months of Treatment
Converted | 87% (248/286) | 80% (226/283)
Not Converted | 1% (4/286) | 3% (8/283)
Lost to Follow-up | 12% (34/286) | 17% (49/283)
Status Through 24 Month Follow-up [Twenty-two (22) deaths occurred during the study; 11 in each treatment group.]
Relapsed | 12% (29/248) | 7% (15/226)
Sputum Negative | 57% (142/248) | 64% (145/226)
Lost to Follow-up | 31% (77/248) | 29% (66/226)

Risk of relapse was greater in the group treated with the PRIFTIN combination. Higher relapse rates were associated with a lower rate of compliance as well as a failure to convert sputum cultures at the end of the initial 2-month treatment phase. Relapse rates were also higher for males in both regimens. Relapse in the PRIFTIN group was not associated with development of monoresistance to rifampin.

The second trial was randomized, open-label performed in 1075 HIV-negative and HIV-positive patients with active pulmonary tuberculosis. Patients with culture-positive, drug-susceptible pulmonary tuberculosis who had completed the initial 2-month phase of treatment with 4 drugs (rifampin, isoniazid, pyrazinamide, and either ethambutol or streptomycin) under direct observation were randomly assigned to receive either PRIFTIN 600 mg and isoniazid 15 mg/kg (max 900 mg) once weekly or rifampin 10 mg/kg (max 600 mg) and isoniazid 15 mg/kg (max 900 mg) twice weekly for the 4 month continuation phase. Study drugs were given under direct observation therapy in both groups.

In the PRIFTIN group, 502 HIV-negative and 36 HIV-positive patients were randomized and in the rifampin group 502 HIV-negative and 35 HIV-positive patients were randomized to treatment. Enrollment of HIV-infected patients was stopped when 4 of 36 patients in the PRIFTIN combination group relapsed with isolates that were rifampin resistant.

Table 9 below contains assessments of sputum conversion at the end of treatment (6 months total: 2 months of initial and 4 months of randomized continuation treatment) and relapse rates at the end of follow-up (24 months) in all HIV-negative patients randomized to treatment. Positive culture was based on either one sputum sample with >10 colonies on solid media OR at least 2 positive sputum samples on liquid or solid media. However, only one sputum sample was collected at each visit in a majority of patients.

Table 9: Clinical Outcome in HIV Negative Patients with Active Pulmonary Tuberculosis (Trial 2)
 | PRIFTIN Combination Treatment % (n/N) | Rifampin Combination Treatment % (n/N)
Status at End of 4 Months Continuation Phase
Treatment Response [Treatment response was defined as subjects who had two negative sputum cultures after 16 doses of rifampin and isoniazid or after 8 doses of PRIFTIN and isoniazid, and remained sputum negative through the end of continuation phase therapy.] | 93.8% (471/502) | 91% (457/502)
Not Converted | 1% (5/502) | 1.2% (6/502)
Did Not Complete Treatment [Due to drug toxic effects, non-adherence, withdrawal of consent, receipt of non-study regimen, other.] | 4.2% (21/502) | 7% (35/502)
Deaths | 1% (5/502) | 0.8% (4/502)
Status Through 24 Month Follow-up:
Relapsed | 8.7% (41/471) | 4.8% (22/457)
Sputum Negative | 79.4% (374/471) | 80.1% (366/457)
Lost to Follow-up | 7.9% (37/471) | 9.8% (45/457)
Deaths | 4% (19/471) | 5.3% (24/457)

In HIV-negative patients, higher relapse rates were seen in patients with a positive sputum culture at 2 months (i.e., at the time of study randomization), cavitation on chest x-ray, and bilateral pulmonary involvement.

Sixty-one HIV-positive patients were assessed for relapse. The rates of relapse were 16.7% (5/30) in the PRIFTIN group and 9.7% (3/31) in the rifampin group. In HIV-positive patients, 4 of the 5 relapses in the PRIFTIN combination group involved M. tuberculosis strains with rifampin monoresistance. No relapse strain in the twice weekly rifampin/isoniazid group acquired drug resistance.

The death rate among all study participants did not differ between the two treatment groups.

14.2 Latent Tuberculosis Infection

A multicenter, prospective, open-label, randomized, active-controlled trial compared the effectiveness of 12 weekly doses of PRIFTIN in combination with isoniazid (3RPT/INH arm) administered by directly observed therapy to 9 months of self-administered daily isoniazid (9INH arm). The trial enrolled patients two years of age or older with positive tuberculin skin test and at high risk for progression to tuberculosis disease. Enrolled patients included those having close contact with a patient with active tuberculosis disease, recent (within two years) conversion to a positive tuberculin skin test, HIV-infection, or fibrosis on chest radiograph. PRIFTIN was dosed by weight, for a maximum of 900 mg weekly. Isoniazid mg/kg dose was determined by age, for a maximum of 900 mg weekly in the 3RPT/INH arm and 300 mg daily in the 9INH arm [see Dosage and Administration (2.2)].

The outcome measure was the development of active tuberculosis disease, defined as culture-confirmed tuberculosis in adults and culture-confirmed or clinical tuberculosis in pediatric patients less than 18 years of age, at 33 months after trial enrollment. Patients who were found after enrollment to be ineligible because they had active tuberculosis disease, were contacts of a source case with culture-negative or drug-resistant tuberculosis disease cases or no information regarding susceptibility of M. tuberculosis, and young pediatric patients lacking a positive TST on initial and repeat testing were excluded from the analysis.

Active tuberculosis disease developed in 5 of 3074 randomized patients in the 3RPT/INH group (0.16%) versus 10 of 3074 patients in 9INH group (0.32%), for a difference in cumulative rates of 0.17%, 95% CI (-0.43, 0.09) (Table 10).

Table 10: Outcomes in Randomized Patients at 33 Months Post Enrollment [Similar results were observed when all enrolled patients were included in the analysis.]
Outcome | 3RPT/INH (n=3074) | 9INH (n=3074) | Difference [Rate in the 3RPT/INH group minus the rate in the 9INH group.] , 95% CI
Tuberculosis n (%) | 5 (0.16) | 10 (0.32) | -0.16 (-0.42, 0.01)
Cumulative TB Rate (%) | 0.17 | 0.35 | -0.17 (-0.43, 0.09)
Deaths | 22 (0.72) | 35 (1.14) | -0.42 (-0.91, 0.06)
Lost to Follow-Up | 320 (10.41) | 357 (11.61) | -1.20 (-2.77, -0.36)

The proportion of patients completing treatment was 81.2% in the 3RPT/INH group and 68.3% in the 9INH group for a difference (3RPT/INH-9INH) of 12.8% 95% CI (10.7, 15.0).

In the 9INH treatment group, two of the thirteen culture-confirmed cases were found to be isoniazid-monoresistant. In the 3RPT/INH treatment group, one of the seven cases was rifampin-resistant, isoniazid-susceptible M. bovis infection.

Pediatric substudy

Enrollment of pediatric patients was extended after the overall target number of patients was attained in the main study. Data from both the main study and the extension were pooled resulting in an eligible population for analysis of 375 pediatric patients in the 3RPT/INH arm and 367 in the 9INH arm.

One child in the 9INH group developed tuberculosis (1/367, cumulative rate 0.32%) versus zero tuberculosis cases in the 3RPT/INH group (0/375) at 33 months post enrollment. The proportion of patients completing treatment in the 3RPT/INH and the 9INH groups was 87.5% and 79.6% respectively for a difference of 7.9%, 95% CI (2.5, 13.2).

HIV substudy

Enrollment of HIV-positive patients was extended after the overall target number of patients was attained in the main study. Data from both the main study and the extension were pooled resulting in an eligible population for analysis of 206 patients in the 3RPT/INH group and 193 in the 9INH group. Tuberculosis disease developed in 2/206 patients in the 3RPT/INH group (cumulative rate, 1.01%) and in 6/193 patients in the 9INH group (cumulative rate, 3.45%). The proportion of patients completing treatment in the 3RPT/INH and 9INH groups was 88.8% and 63.7%, respectively for a difference of 25.1%, 95% CI (16.8, 32.9).

16 HOW SUPPLIED/STORAGE AND HANDLING

How Supplied

PRIFTIN is supplied as 150 mg round normal convex dark-pink film-coated tablets debossed "F" on one side of tablet packaged in aluminum formable foil blister strips.

Carton of 24 tablets (3 strips of 8 tablets) NDC 0088-2102-24

Storage

Store at 25°C (77°F); excursions permitted 15–30°C (59–86°F) (see USP Controlled Room Temperature). Protect from excessive heat and humidity.

17 PATIENT COUNSELING INFORMATION

Advise patient to read FDA-approved patient labeling (Medication Guide).

Treatment Adherence

Emphasize the importance of compliance with the full course of therapy, and the importance of not missing any doses of PRIFTIN or companion medications in the treatment of active pulmonary tuberculosis or the treatment of latent tuberculosis infection.

Hypersensitivity Reactions

Inform patients that PRIFTIN may cause hypersensitivity reactions. Signs and symptoms of this reaction may include a flu-like illness, hypotension, urticaria, angioedema, bronchospasm, conjunctivitis, thrombocytopenia or neutropenia. Anaphylaxis may also occur [see Warnings and Precautions (5.2)].

Inform patients of signs and symptoms of hypersensitivity reactions and advise them to stop the medication and contact their healthcare provider if they experience any of these symptoms.

Severe Cutaneous Adverse Reactions

Advise patients about the signs and symptoms of serious skin manifestations. Instruct patients to stop taking PRIFTIN immediately and promptly report the first signs or symptoms of skin rash, mucosal lesions, or any other sign of hypersensitivity [see Warnings and Precautions (5.3)].

Hepatitis

Instruct patients to stop the medication and notify their physician promptly if they experience any of the following: fever, loss of appetite, malaise, nausea and vomiting, darkened urine, yellowish discoloration of the skin and eyes, and pain or swelling of the joints [see Warnings and Precautions (5.1)].

Paradoxical Drug Reactions

Advise patients to seek medical advice immediately if their symptoms of tuberculosis reappear or worsen [see Warnings and Precautions (5.5)].

Drug Interactions

Rifapentine may increase the metabolism and decrease the activity of other drugs that are metabolized by the P450 3A4 and 2C8/9 pathways. Dosage adjustments of the coadministered drugs may be necessary. Advise patients to discuss with their physician any other medications they are taking before starting treatment with PRIFTIN [see Warnings and Precautions (5.6), Drug Interactions (7.1, 7.4)].

Concomitant use of PRIFTIN with protease inhibitors or reverse transcriptase inhibitors may cause a significant decrease in plasma concentrations and loss of therapeutic effect of the protease inhibitor or reverse transcriptase inhibitor [see Warnings and Precautions (5.6) and Drug Interactions (7.4)].

Discoloration of Body Fluids

Inform the patient that PRIFTIN produces a red-orange discoloration of the urine, sweat, sputum, tears, and breast milk. Contact lenses or dentures may be permanently stained [see Warnings and Precautions (5.7)].

Administration with Food

Advise patients to take PRIFTIN with food [see Dosage and Administration (2.3)].

Lactation

Monitor infants exposed to rifapentine through breast milk for signs of hepatotoxicity to include irritability, prolonged unexplained crying, yellowing of the eyes, loss of appetite, vomiting, and changes in color of the urine (darkening) or stool (lightening, pale or light brown) [see Use in Specific Populations (8.2)].

Contraception

Advise patients that use of PRIFTIN may reduce the efficacy of hormonal contraceptives. Advise patients using hormonal contraceptives to use an alternative non-hormonal contraceptive method or add a barrier method of contraception during treatment [see Warning and Precautions (5.6), Drug Interactions (7.3), and Use in Specific Populations (8.3)].

sanofi-aventis U.S. LLC
Morristown, NJ 07960
A SANOFI COMPANY
©2026 sanofi-aventis U.S. LLC

Medication Guide
PRIFTIN (prif - tin)
(rifapentine)
Tablets

Read this Medication Guide before you start taking PRIFTIN and each time you get a refill. There may be new information. This information does not take the place of talking with your doctor about your medical condition or your treatment.

What is the most important information I should know about PRIFTIN?

PRIFTIN may cause serious side effects, including:

- Liver problems. PRIFTIN may cause serious liver problems. Your doctor may do a blood test to check your liver function before and while you take PRIFTIN. Stop taking PRIFTIN and call your doctor right away if you have any of the following signs and symptoms of liver problems:

- nausea
- stomach pain
- tiredness, yellowing skin or whites of your eyes

- vomiting
- loss of appetite
- dark urine

- Allergic reactions and flu-like symptoms. Allergic reactions and flu-like symptoms have happened in some people taking PRIFTIN. Signs and symptoms of an allergic reaction may include:

- low blood pressure (hypotension)
- hives
- cough with wheezing

- difficulty breathing
- red eyes (conjunctivitis)
- lower blood platelet levels

Signs and symptoms of a flu-like reaction may include:

- weakness
- nausea and vomiting
- chills
- itching
- shortness of breath
- fainting

- tiredness
- headache
- aches
- sweats
- chest pain
- fast heartbeat

- muscle pain
- fever
- rash
- dizziness
- cough

- Severe skin reactions. Serious skin reactions such as Stevens-Johnson syndrome (SJS) and drug reaction with eosinophilia and systemic symptoms (DRESS) syndrome have happened in some people taking PRIFTIN.
  Stop taking PRIFTIN right away and call your doctor or get emergency help if you have any of the following symptoms:

- rash
- red and painful skin

- peeling or bleeding skin
- sores or blisters on the inside of your mouth or lips

- swollen face, lips, mouth tongue or throat
- flu-like symptoms

What is PRIFTIN?

PRIFTIN is a prescription medicine used with other anti-tuberculosis (TB) medicines to:

- treat active tuberculosis disease of the lung in people age 12 years and older.
- prevent progression of inactive (latent) tuberculosis infection to active tuberculosis disease in people age 2 years and older.

PRIFTIN should not be used:

- alone to treat people with active or latent TB
- in people with active TB who had taken the medicines rifampin or isoniazid in the past and did not respond (resistant)
- in people who had been exposed to patients with TB that cannot be treated with isoniazid or rifampin

PRIFTIN is safe and effective in children older than 2 years of age who have inactive (latent TB), but it is not known if PRIFTIN is safe and effective for use in the treatment of active TB in children under 12 years of age.

Who should not take PRIFTIN?

- Do not take PRIFTIN if you are allergic to a group of medicines called rifamycins.

What should I tell my doctor before taking PRIFTIN?

Before taking PRIFTIN, tell your doctor about all of your medical conditions, including if you:

- have active TB disease.
- know that you have TB that is resistant to treatment with some medicines.
- have HIV infection or taking medicines to treat HIV infection.
- have liver problems.
- have a condition called porphyria.
- are pregnant or planning to become pregnant. It is not known if PRIFTIN will harm your unborn baby.
- are breastfeeding or plan to breastfeed. It is not known if PRIFTIN passes into your breast milk. Talk to your healthcare provider about the best way to feed your baby while taking PRIFTIN.

Tell your doctor about all the medicines you take, including prescription and over-the-counter medicines, vitamins, and herbal supplements.

Using PRIFTIN with other medicines may affect each other causing serious side effects. PRIFTIN may affect the way other medicines work, and other medicines may affect how PRIFTIN works. Especially tell your doctor if you take medicines to treat HIV infection or oral contraceptives.

Ask your doctor or pharmacist for a list of these medicines if you are not sure.

Know the medicines you take. Keep a list of them to show your doctor or pharmacist when you get a new medicine.

How should I take PRIFTIN?

- Take PRIFTIN exactly as your doctor tells you to take it.
  It is important to take all of your PRIFTIN and your other TB medicines. Do not skip doses. Skipping doses may cause PRIFTIN to not work as well and may increase the chance that your TB will not be treatable by PRIFTIN or other medicines.
- Take PRIFTIN with food.
  If you cannot swallow PRIFTIN tablets whole, they can be crushed and mixed with small amount of semisolid food. Be sure to take all of the semisolid food with PRIFTIN in it right away.

What are possible side effects of PRIFTIN?

PRIFTIN may cause serious side effects, including:

- see "What is the most important information I should know about PRIFTIN?"
- relapse of your TB symptoms. Active TB disease may return after improvement (relapse) in some people, especially people who do not take PRIFTIN exactly as their doctor tells them to. It is important that you take PRIFTIN exactly as your doctor tells you to. Your doctor should check you for worsening signs and symptoms of your TB while you take PRIFTIN.
- change in the normal color of your skin, mouth and body fluids. PRIFTIN may cause your skin, teeth, tongue, urine, feces, saliva, sputum, tears, sweat, and breast milk to turn a red-orange color. Contact lenses or dentures may become permanently stained.
- diarrhea. A type of diarrhea called Clostridioides difficile–associated diarrhea (CDAD) may occur during or after taking antibiotics, including PRIFTIN. The severity of CDAD can range from mild diarrhea to severe diarrhea that may cause death (fatal colitis). Tell your doctor right away if you have diarrhea while you take or after you stop taking PRIFTIN.
- worsening of a condition called porphyria.

The most common side effects of PRIFTIN include: allergic reactions and flu-like symptoms; abnormalities such as low red blood cells, low white blood cells, coughing up blood, cough, excessive number of platelets in the blood, increased sweating, high liver function tests, back pain, rash, decreased appetite, joint pain, increased blood urea, and headache.

Tell your doctor if you have any side effect that bothers you or that does not go away. These are not all the possible side effects of PRIFTIN. For more information, ask your doctor or pharmacist.

Call your doctor for medical advice about side effects. You may report side effects to FDA at 1-800-FDA-1088.

How should I store PRIFTIN?

- Store PRIFTIN at room temperature between 68°F to 77°F (20°C to 25°C).
- Keep PRIFTIN dry and away from heat.
- Keep PRIFTIN and all medicines out of reach of children.

General information about the safe and effective use of PRIFTIN.

Medicines are sometimes prescribed for purposes other than those listed in a Medication Guide. Do not use PRIFTIN for a condition for which it was not prescribed. Do not give PRIFTIN to other people, even if they have the same symptoms you have. It may harm them.

This Medication Guide summarizes the most important information about PRIFTIN. If you would like more information, talk with your doctor. You can ask your doctor or pharmacist for information about PRIFTIN that is written for healthcare professionals.

What are the ingredients in PRIFTIN?

Active ingredient: rifapentine

Inactive ingredients: calcium stearate, disodium EDTA, FD&C Blue No. 2 aluminum lake, hydroxypropyl cellulose, hypromellose USP, microcrystalline cellulose, polyethylene glycol, pregelatinized starch, propylene glycol, sodium ascorbate, sodium lauryl sulfate, sodium starch glycolate, synthetic red iron oxide, and titanium dioxide

Manufactured by: sanofi-aventis U.S. LLC, Morristown, NJ 07960
For more information, go to www.sanofi.us or call 1-800-633-1610, and select option 1.

This Medication Guide has been approved by the U.S. Food and Drug Administration.

Revised: December 2025

PRINCIPAL DISPLAY PANEL - 150 mg Tablet Blister Pack Carton

NDC 0088-2102-24

PRIFTIN®
RIFAPENTINE

150 mg per tablet

Dispense with Medication Guide

24 Tablets
Three 8-Tablet
Blister Strips

sanofi